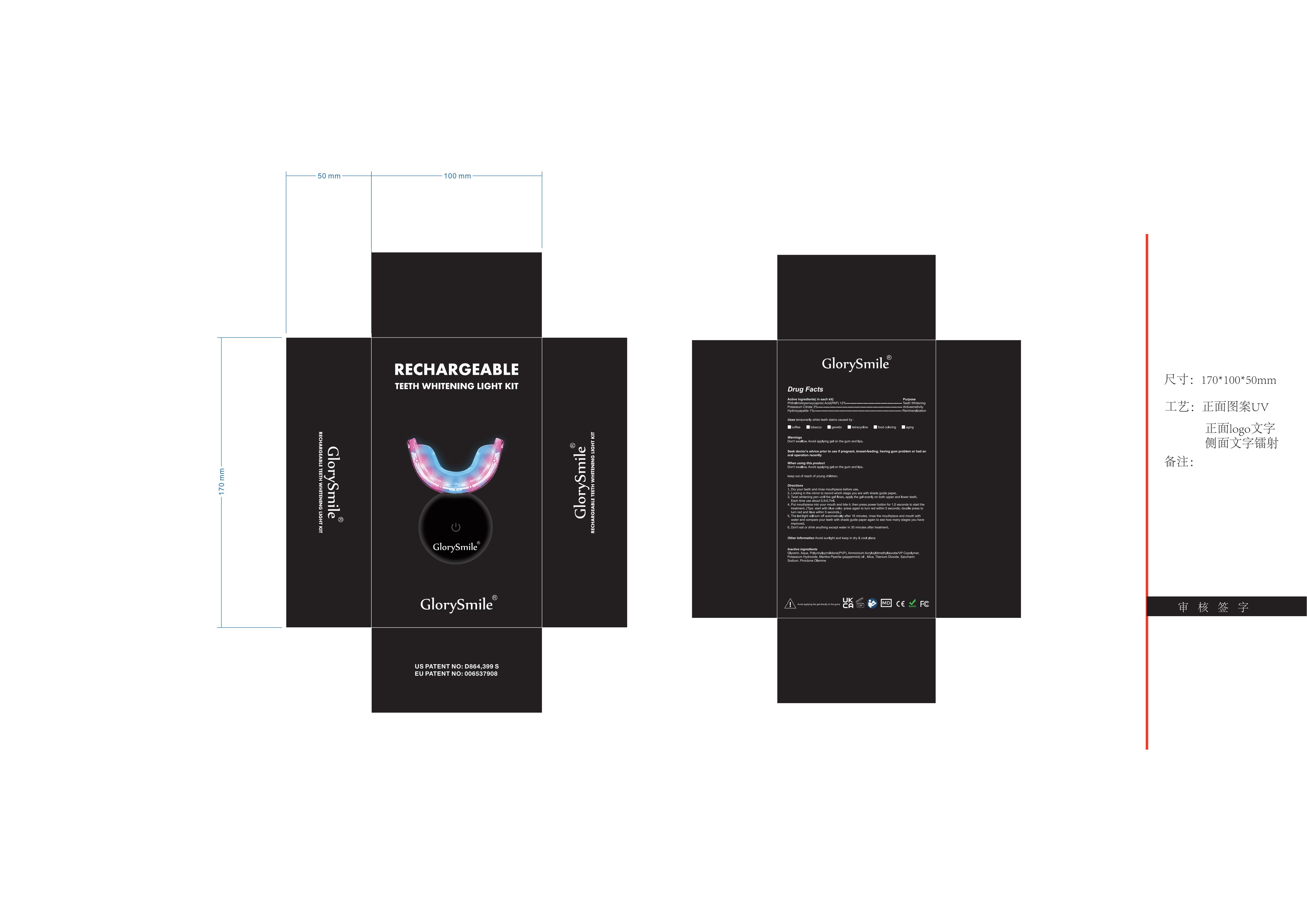 DRUG LABEL: Teeth Whitening Kit
NDC: 83778-002 | Form: CREAM
Manufacturer: Jiangxi Dentalbright Technology Co., Ltd
Category: otc | Type: HUMAN OTC DRUG LABEL
Date: 20241220

ACTIVE INGREDIENTS: TRIBASIC CALCIUM PHOSPHATE 1 g/100 mL; PHTHALIMIDOPEROXYCAPROIC ACID 12 g/100 mL; POTASSIUM CITRATE 3 g/100 mL
INACTIVE INGREDIENTS: WATER; POVIDONE; POTASSIUM HYDROXIDE; PEPPERMINT OIL; MICA; SACCHARIN SODIUM; TITANIUM DIOXIDE; PIROCTONE OLAMINE; SODIUM ACRYLOYLDIMETHYLTAURATE; GLYCERIN

83778-002 Update

Active Ingredient

Phthalimidoperoxycaproic Acid(PAP)
Potassium Citrate
Hydroxyapatite

Purpose

Teeth whitening, anti-sensitivity, remineralization

Use

Teeth stains from coffee, tobacco, genetic, tetracycline, food coloring, aging and other factors that may cause discoloration.

Warnings

Don't swallow. Avoid applying gel on the gum and lips.

Do not use

1. Not suitable for ceramic or false teeth.
2. Not suitable for teeth discoloration caused by lesion or medicine.
3. Not suitable for severe tetracycline and decayed teeth.
4. Not suitable for defective enamel, exerted dentin and damaged teeth.
5. Not suitable for children under 16 years old

When Using

Don't swallow. Avoidapplying gel on the gum and lips.

Stop Use

Stop treatment when feel severe pain

Ask Doctor

Seek doctor's advice prior to use if pregnant, breast-feeding, having gum problem or had an oral operation recently

Keep Oot Of Reach Of Children

Keep out of reach of children.

Directions

1. Dry your teeth and rinse mouthpiece before use.
2. Looking in the mirror to record which stage you are with shade guide paper.
3. Twist whitening pen until the gel flows. apply the gel evenly on both upper and lower teeth. Each time use about 0.5-0.7ml.
4. Put mouthpiece into your mouth and bite it, then press power button for 1.5 seconds to start the treatment. (Tips: start with blue color, press again to turn red within 5 seconds; double press to turn red and blue within 5 seconds.)
5. The led light will turn off automatically after 16 minutes, rinse the mouthpiece and mouth with water and compare your teeth with shade guide paper again to see how many stages you have improved.
6. Don't eat or drink anything except water in 30 minutes after treatment.

Other information

Avoid sunlight and keep in dry & cool place

Inactive ingredients

Glycerin、Aqua、Polyvinylpyrrolidone(PVP)、Ammonium
Acryloyldimethyltaurate/VP Copolymer、Potassium Hydroxide、Mentha Piperita (peppermint) oil 、Mica、Titanium Dioxide、Saccharin Sodium、Piroctone Olamine